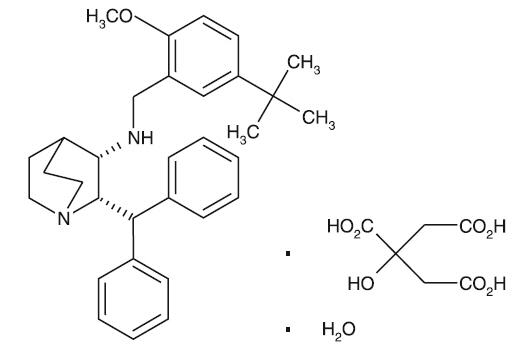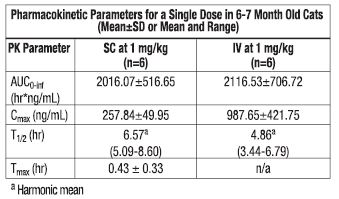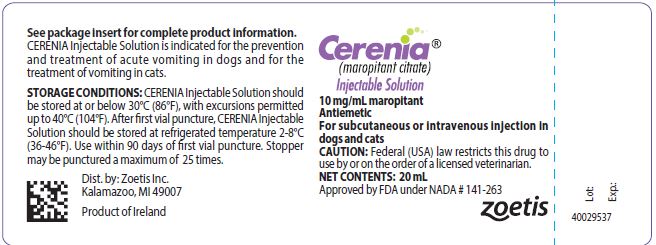 DRUG LABEL: Cerenia
NDC: 54771-8179 | Form: INJECTION
Manufacturer: Zoetis Inc.
Category: animal | Type: PRESCRIPTION ANIMAL DRUG LABEL
Date: 20250807

ACTIVE INGREDIENTS: MAROPITANT CITRATE 10 mg/1 mL
INACTIVE INGREDIENTS: SULFOBUTYLETHER .BETA.-CYCLODEXTRIN 63 mg/1 mL; METACRESOL 3.3 mg/1 mL; WATER

Cerenia®
(maropitant citrate)
Injectable Solution

Antiemetic

For subcutaneous injection in dogs and cats

CAUTION

Federal law restricts this drug to use by or on the order of a licensed veterinarian.

DESCRIPTION

Maropitant is a neurokinin (NK1) receptor antagonist that blocks the pharmacological action of substance P in the central nervous system (CNS). Maropitant is the non-proprietary designation for a substituted quinuclidine. The empirical formula is C32H40N2O C6H8O7 H2O and the molecular weight 678.81. The chemical name is (2S,3S)-2-benzhydryl-N-(5-tert-butyl-2- methoxybenzyl) quinuclidin-3-amine citrate monohydrate. Each mL of CERENIA Injectable Solution contains 10 mg maropitant, 63 mg sulphobutylether-beta-cyclodextrin, 3.3 mg meta-cresol and water for injection.

The chemical structure of maropitant citrate is:

INDICATIONS

Dogs: CERENIA (maropitant citrate) Injectable Solution is indicated for the prevention and treatment of acute vomiting in dogs.

Cats: CERENIA (maropitant citrate) Injectable Solution is indicated for the treatment of vomiting in cats.

DOSAGE AND ADMINISTRATION

Use of refrigerated product may reduce the pain response associated with subcutaneous injection.

Dogs

For Prevention and Treatment of Acute Vomiting in Dogs:
Dogs 2-4 Months of Age: Administer CERENIA Injectable Solution subcutaneously at 1 mg/kg (0.45 mg/lb) equal to 0.1 mL/kg (0.1 mL/2.2 lb) of body weight once daily for up to 5 consecutive days.

Dogs 4 months of Age and Older: Administer CERENIA Injectable Solution intravenously over 1-2 minutes or subcutaneously at 1 mg/kg (0.45 mg/lb) equal to 0.1 mL/1 kg (1 mL/22 lb) of body weight once daily for up to 5 consecutive days.

In dogs that are actively vomiting, it is recommended to initiate treatment with CERENIA Injectable Solution. Thereafter, CERENIA Tablets may be used for the prevention of acute vomiting at 2 mg/kg once daily. (See CERENIA Tablets package insert for complete prescribing information).

For Prevention of Vomiting in Dogs 4 months of Age and Older Caused by Emetogenic Medications or Chemotherapeutic Agents: Administer CERENIA Injectable Solution intravenously over 1-2 minutes or subcutaneously at 1 mg/kg (0.45 mg/lb) of body weight one time, 45-60 minutes prior to use of emetogenic medications or chemotherapeutic agents

Cats

For Treatment of Vomiting in Cats 4 Months of Age and Older: Administer CERENIA Injectable Solution intravenously over 1-2 minutes or subcutaneously at 1 mg/kg (0.45 mg/lb) equal to 0.1 mL/kg (0.1 mL/2.2 lb) of body weight once daily for up to 5 consecutive days.

The underlying cause of acute vomiting should be identified and addressed in dogs and cats that receive CERENIA Injectable Solution. If vomiting persists despite treatment, the case should be re-evaluated.

WARNINGS

Not for use in humans. Keep out of reach of children. In case of accidental injection or exposure, seek medical advice. Topical exposure may elicit localized allergic skin reactions in some individuals. Repeated or prolonged exposure may lead to skin sensitization. In case of accidental skin exposure, wash with soap and water. CERENIA is also an ocular irritant. In case of accidental eye exposure, flush with water for 15 minutes and seek medical attention.

In puppies younger than 11 weeks of age, histological evidence of bone marrow hypocellularity was observed at higher frequency and greater severity in puppies treated with CERENIA compared to control puppies. In puppies 16 weeks and older, bone marrow hypocellularity was not observed (see ANIMAL SAFETY).

PRECAUTIONS

The safe use of CERENIA Injectable Solution has not been evaluated in dogs or cats with gastrointestinal obstruction or that have ingested toxins.

Use with caution in patients with hepatic dysfunction because CERENIA Injectable Solution is metabolized by CYP3A, CYP2D15(dogs) and CYP1A (cats) enzymes (see Pharmacokinetics). The influence of concomitant drugs that may inhibit the metabolism of CERENIA Injectable Solution has not been evaluated. CERENIA Injectable Solution is highly protein bound. Use with caution with other medications that are highly protein bound. The concomitant use of CERENIA Injectable Solution with other protein bound drugs has not been studied in dogs or cats. Commonly used protein bound drugs include NSAIDs, cardiac, anticonvulsant, and behavioral medications. Drug compatibility should be monitored in patients requiring adjunctive therapy.

The safe use of CERENIA Injectable Solution has not been evaluated in dogs or cats used for breeding, or in pregnant or lactating bitches or queens.

ADVERSE REACTIONS

DOGS

In a US field study for the prevention and treatment of vomiting associated with administration of cisplatin for cancer chemotherapy, the following adverse reactions were reported in 77 dogs treated with CERENIA Injectable Solution at 1 mg/kg subcutaneously or 41 dogs treated with placebo:

Frequency of Adverse Reactions by Treatment
Adverse Reaction | Placebo (n=41) |  | CERENIA (n=77)
Adverse Reaction | # dogs | % occur | # dogs | % occur
Diarrhea | 1 | 2.4 | 6 | 7.8
Anorexia | 0 | 0 | 4 | 5.2
Injection site reaction (swelling, pain upon injection) | 0 | 0 | 3 | 4
Lethargy | 1 | 2.4 | 2 | 2.6

The following adverse reactions were reported during the course of a US field study for the prevention and treatment of acute vomiting in dogs treated with 1 mg/kg CERENIA Injectable Solution subcutaneously and/or CERENIA Tablets at a minimum of 2 mg/kg orally once daily for up to 5 consecutive days:

Frequency of Adverse Reactions by Treatment
Adverse Reaction | Placebo (n=69) |  | CERENIA (n=206)
Adverse Reaction | # dogs | % occur | # dogs | % occur
Death during study | 4 | 5.8 | 10 | 4.9
Euthanized during study | 0 | 0 | 2 | 1
Diarrhea | 6 | 8.7 | 8 | 3.9
Hematochezia/bloody stool | 5 | 7.2 | 4 | 1.9
Anorexia | 2 | 2.9 | 3 | 1.5
Otitis/Otorrhea | 0 | 0 | 3 | 1.5
Endotoxic Shock | 1 | 1.4 | 2 | 1
Hematuria | 0 | 0 | 2 | 1
Excoriation | 0 | 0 | 2 | 1

Other clinical signs were reported but were <0.5% of dogs.

Adverse reactions seen in a European field study included ataxia, lethargy and injection site soreness in one dog treated with CERENIA Injectable Solution.

Post-Approval Experience (Rev. 2015)

The following adverse events are based on post-approval adverse drug experience reporting. Not all adverse events are reported to FDA CVM. It is not always possible to reliably estimate the adverse event frequency or establish a causal relationship to product exposure using these data.

The following adverse events reported for dogs are listed in decreasing order of reporting frequency for CERENIA Injectable Solution: Pain/vocalization upon injection, depression/lethargy, anorexia, anaphylaxis/anaphylactoid reactions (including swelling ofthe head/face), ataxia, convulsions, hypersalivation, tremors, fever, dyspnea, collapse/loss of consciousness, recumbency, injection site reactions (swelling, inflammation) and sedation.

Cases of death (including euthanasia) have been reported.

CATS

The following adverse reactions were reported during the course of a US field study for the treatment of vomiting in cats treated with 1 mg/kg CERENIA Injectable Solution subcutaneously once daily for up to five consecutive days:

Frequency of Adverse Reactions by Treatment
Adverse Reaction | Placebo (n=62) |  | CERENIA (n=133)
Adverse Reaction | # cats | % occur | # cats | % occur
Moderate Response to Injection [The clinician observed and graded each cat's response to injection.] , [Cat objected to the injection by retreating and vocalizing] | 1 | 1.6 | 30 | 22.6
Significant Response to Injection, [Cat objected to the injection by retreating, hissing, scratching, and vocalization] | 1 | 1.6 | 15 | 11.3
Fever/Pyrexia | 2 | 3.2 | 2 | 1.5
Dehydration | 0 | 0 | 3 | 2.3
Lethargy | 0 | 0 | 2 | 1.5
Anorexia | 0 | 0 | 1 | 0.8
Hematuria | 0 | 0 | 1 | 0.8
Hypersalivation | 0 | 0 | 1 | 0.8
Injection site swelling | 1 | 1.6 | 0 | 0

^1The clinician observed and graded each cat’s response to injection.

^2 Cat objected to the injection by retreating and vocalizing

^3 Cat objected to the injection by retreating, hissing, scratching, and vocalization

Post-Approval Experience (Rev. 2015)

The following adverse events are based on post-approval adverse drug experience reporting. Not all adverse events are reported to FDA CVM. It is not always possible to reliably estimate the adverse event frequency or establish a causal relationship to product exposure using these data.

The following adverse events reported for cats are listed in decreasing order of reporting frequency for CERENIA Injectable Solution: Depression/lethargy, anorexia, hypersalivation, pain/vocalization upon injection, dyspnea, ataxia, fever, recumbency, vomiting, panting, convulsion, and muscle tremor.

Cases of death (including euthanasia) have been reported.

To report suspected adverse events, for technical assistance or to obtain a copy of the SDS, contact Zoetis Inc. at 1-888-963-8471 or www.zoetis.com.
For additional information about adverse drug experience reporting for animal drugs, contact FDA at 1-888-FDA-VETS or www.fda.gov/reportanimalae.

CLINICAL PHARMACOLOGY:

Pharmacodynamics:

Vomiting is a complex process coordinated centrally by the emetic center which consists of several brainstem nuclei (area postrema, nucleus tractus solitarius, dorsal motor nucleus of the vagus) that receive and integrate sensory stimuli from central and peripheral sources and chemical stimuli from the circulation and the cerebro-spinal fluid. Maropitant is a neurokinin 1 (NK1) receptor antagonist which acts by inhibiting the binding of substance P, a neuropeptide of the tachykinin family. Substance P is found in significant concentrations in the nuclei comprising the emetic center and is considered the key neurotransmitter involved in emesis.1 By inhibiting the binding of substance P within the emetic center, maropitant provides broad-spectrum effectiveness against neural (central) and humoral (peripheral) causes of vomiting. In vivo model studies in dogs have shown that maropitant has antiemetic effectiveness against both central and peripheral emetogens including apomorphine, cisplatin, and syrup of ipecac.

Pharmacokinetics:

CERENIA Injectable Solution is formulated using sulphobutyletherß-cyclodextrin (SBECD), which exhibits enhanced binding to maropitant at refrigerated temperatures. The enhanced binding affinity reverses rapidly upon warming.

DOGS

The pharmacokinetic (PK) characterization associated with maropitant after a single oral (PO), intravenous (IV), or subcutaneous (SC) dose administration in adult Beagle dogs is provided in the table below.

Pharmacokinetic Parameters in Beagle Dogs(Mean ±SD or Mean and Range)
PKParameter | SC at 1 mg/kg (n=8) | IV at 1 mg/kg (n=8) | PO at 2 mg/kg (n=8) | PO at 8 mg/kg (n=8)
AUC0-inf (hr*ng/mL) | 759.08±189.49 | 693.83±137.25 | 561±322 | 7840±5600
Cmax (ng/mL) | 102.99±46.06 | 296.62±60.77 | 81±32 | 776±604
T1/2 (hr) | 8.84a; (6.15-20.48) | 6.85a; (4.87 -11.30) | 4.03 (2.48–7.09) | 5.46 (3.39–7.65)
Tmax (hr) | 0.56±0.40 | n/a | 1.9±0.5 | 1.7±0.7

a Harmonic mean

The absolute bioavailability of maropitant was much higher following SC injection (91% at 1 mg/kg) than after PO administration (24% at 2 mg/kg). Oral bioavailability may be underestimated due to the presence of nonlinear kinetics and the resulting longer T1/2 seen after intravenous (IV) administration. Although hepatic firstpass metabolism contributed to the relatively low bioavailability after an oral dose, prandial status does not significantly affect the extent of oral bioavailability. Greater than dose-proportional drug exposure can be expected with an increase in dose (1–16 mg/kg PO). Systemic clearance of maropitant following IV administration was 1499.13 mL/hr/kg at a dose of 1 mg/kg. An accumulation ratio of 1.5 was observed following once-daily use of maropitant for five consecutive days at 1 (SC) or 2 mg/kg (PO). Urinary recovery of maropitant and its major metabolitewas minimal (<1% each). The hepatic metabolism of maropitant involves two cytochrome P-450 isoenzymes: CYP2D15 and CYP3A12. Based on in vitro enzyme kinetics data, it is believed that the non-linear kinetics may be partially associated with saturation of the low capacity enzyme (CYP2D15). However as doses increase (20–50 mg/kg PO), dose proportionality is re-established.

Based upon in vitro enzyme kinetics, involvement of a high capacity enzyme (CYP3A12) may contribute to this return to dose linearity. Plasma protein binding of maropitant was high (99.5%).

Based on differences in plasma trough concentrations from a single study, the exposure of 10 week old puppies to maropitant may be lower than that observed in adult dogs, particularly after doses of 1 or 2 mg/kg.

CATS

The pharmacokinetic characterization associated with maropitant after a single subcutaneous (SC) or intravenous (IV) dose administration in cats is provided in the table below.

Pharmacokinetic Parameters for a Single Dose in 6-7 Month Old Cats

(Mean±SD or Mean and Range)

There appears to be an age-related effect on the pharmacokinetics of maropitant in cats; kittens (4 months) have a higher clearance than adults. In multiple IV and SC studies, the mean maropitant half-life in kittens (4-7 months old) is 7.83 hours, compared to 17.2 hours in adults. The mean bioavailability of maropitant after subcutaneous administration in cats was 91.3%. The mean total body clearance (CL) and volume of distribution at steady-state (Vss) determined after IV administration of 1.0 mg/kg to 6 cats was 510 (388 to 603) mL/hr/kg and 2.3 (1.4 to 3.6) L/kg, respectively. Maropitant displays linear kinetics when administered SC within the 0.25–3 mg/kg dose range. Following SC administration of once daily doses of 1 mg/kg body weight for 5 consecutive days, accumulation was 250%. Maropitant undergoes cytochrome P450 (CYP) metabolism in the liver. CYP1A and CYP3A-related enzymes were identified as the feline isoforms involved in the hepatic biotransformation of maropitant. Renal and fecal clearances are minor routes of elimination for maropitant, with less than 1% of a 1 mg/kg SC dose appearing in the urine or feces as maropitant. For the major metabolite, 10.4% of the maropitant dose was recovered in urine and 9.3% in feces. Plasma protein binding of maropitant in cats was estimated to be 99.1%.

EFFECTIVENESS

DOGS

In laboratory model studies, CERENIA Injectable Solution administered at 1 mg/kg in Beagle dogs reduced the number of emetic events associated with established neural (central) and humoral (peripheral) stimuli. Following administration of apomorphine (central emetic stimuli), vomiting was observed in 16.7% (2 of 12) of dogs treated with CERENIA Injectable Solution and 83.3% (10 of 12) of placebo-treated dogs. Following administration of syrup of ipecac (peripheral emetic stimuli) vomiting was observed in 25% (3 of 12) of dogs treated with CERENIA Injectable Solution and in 100% (12 of 12) of dogs treated with placebo.

In a study of veterinary cancer patients, dogs were treated with CERENIA Injectable Solution or placebo either 1 hour prior to cisplatin (prevention) or after the first vomiting episode following cisplatin (treatment) and monitored for 5 hours. In the groups evaluated for prevention of vomiting, 94.9% (37/39) of the dogs administered CERENIA Injectable Solution and 4.9% (2/41) of the dogs administered placebo did not vomit. In the groups evaluated for treatment, 21% (8/38) of the dogs administered CERENIA Injectable Solution and 5.1% (2/39) of the dogs administered placebo had no further episodes of vomiting following treatment.

Frequency Distribution of Numbers of Vomiting Episodes For Treatment: Number of Vomiting Episodes Post Injection. For Prevention: Total Number of Vomiting Episodes.
Number of Vomiting Episodes | Dogs with Vomiting Episodes [Dogs that exhibited an unacceptable level of vomiting (6 events) were withdrawn from the study and treated with another antiemetic.] (% of Dogs)
Number of Vomiting Episodes | Treatment of Vomiting |  | Prevention of Vomiting
Number of Vomiting Episodes | Placebo (n=39 [There were initially 41 and 42 dogs treated with either placebo or CERENIA Injectable Solution, respectively. However, if a dog did not vomit following cisplatin therapy, it did not receive a post-cisplatin treatment with either placebo or CERENIA, and hence it was not considered in the therapeutic evaluation.]) | CERENIA (n=38) | Placebo (n=41) | CERENIA (n=39)
0 | 2 (5.1) | 8 (21.1) | 2 (4.9) | 37 (94.9)
1 | 3 (7.7) | 7 (18.4) | 2 (4.9) | 1 (2.6)
2 | 4 (10.3) | 6 (15.8) | 3 (7.3) | 1 (2.6)
3 | 3 (7.7) | 6 (15.8) | 4 (9.8) | 0 (0)
4 | 4 (10.3) | 4 (10.5) | 3 (7.3) | 0 (0)
5 | 2 (5.1) | 5 (13.2) | 4 (9.8) | 0 (0)
6 | 14 (35.9) | 1 (2.6) | 1 (2.4) | 0 (0)
7 | 2 (5.1) | 1 (2.6) | 12 (29.3) | 0 (0)
8 | 2 (5.1) | 0 (0) | 5 (12.2) | 0 (0)
9 | 2 (5.1) | 0 (0) | 2 (4.9) | 0 (0)
10 | 0 (0) | 0 (0) | 2 (4.9) | 0 (0)
11 | 1 (2.6) | 0 (0) | 0 (0) | 0 (0)
12 | NA | NA | 1 (2.4) | 0 (0)

* Dogs that exhibited an unacceptable level of vomiting (6 events) were withdrawn from the study and treated with another antiemetic.
** There were initially 41 and 42 dogs treated with either placebo or CERENIA Injectable Solution, respectively. However, if a dog did not vomit following cisplatin therapy, it did not receive a post-cisplatin treatment with either placebo or CERENIA Injectable Solution, and hence it was not considered in the therapeutic evaluation.

In a study of 275 canine patients presented to veterinary hospitals with a history of acute vomiting, dogs were initially administered CERENIA Injectable Solution or placebo on Day 0. Following the initial dose, dogs allocated to the CERENIA group were treated with either CERENIA Tablets at a minimum of 2 mg/kg orally or Injectable Solution at 1 mg/kg subcutaneously once daily at the discretion of the clinician. Dogs allocated to the placebo group were treated using either an injectable placebo solution or placebo tablets once daily at the discretion of the clinician. Of the 199 dogs included in the analysis for effectiveness, 27 of 54 dogs (50%) in the placebo group displayed vomiting at some time during the study and 31 of 145 dogs (21.4%) in the CERENIA-treated group displayed vomiting during the study period.

Percent of Vomiting for Each Study Day, Based Upon Treatment and Route of Administration.
Days | Treatment | Route | # dogs | # vomited | % vomited
Day 0 | Placebo (54) | SC | 54 | 15 | 28%
Day 0 | CERENIA (145) | SC | 145 (143 [2 dogs administered CERENIA were not observed on Day 0. Their vomiting status was unknown. 143 was used in the denominator for % vomited.]) | 14 | 10%
Day 1 | Placebo (45) | PO | 22 | 3 | 14%
Day 1 | Placebo (45) | SC | 23 | 16 | 70%
Day 1 | CERENIA (108) | PO | 67 | 2 | 3%
Day 1 | CERENIA (108) | SC | 41 | 16 | 39%
Day 2 | Placebo (16) | PO | 7 | 2 | 29%
Day 2 | Placebo (16) | SC | 9 | 6 | 67%
Day 2 | CERENIA (37) | PO | 24 | 0 | 0%
Day 2 | CERENIA (37) | SC | 13 | 8 | 62%
Day 3 | Placebo (6) | PO | 2 | 0 | 0%
Day 3 | Placebo (6) | SC | 4 | 1 | 25%
Day 3 | CERENIA (21) | PO | 14 | 0 | 0%
Day 3 | CERENIA (21) | SC | 7 | 5 | 71%
Day 4 | Placebo (2) | PO | 1 | 0 | 0%
Day 4 | Placebo (2) | SC | 1 | 1 | 100%
Day 4 | CERENIA (7) | PO | 5 | 0 | 0%
Day 4 | CERENIA (7) | SC | 2 | 1 | 50%
Day 5 | CERENIA (1) | SC | 1 | 0 | 0%

* 2 dogs administered CERENIA were not observed on Day 0. Their vomiting status was unknown. 143 was used in the denominator for % vomited.

In US field studies in veterinary patients, CERENIA Injectable Solution and Tablets were well tolerated in dogs presenting with various clinical conditions including parvovirus, gastroenteritis, and renal disease. There were no notable differences in mean laboratory values between CERENIA-treated and placebo-treated patients.

CERENIA Injectable Solution was used safely in dogs receiving other frequently used veterinary products such as fluid and electrolyte replacement solutions, antimicrobial agents, vaccines, antacids, and antiparasitic agents.

In a laboratory study, thirty-one dogs were subcutaneously administered CERENIA Injectable Solution or saline, at 1 mL/10 kg body weight, 45 minutes prior to administration of an opioid analgesic. Following administration of the opioid analgesic, none of the CERENIA Injectable Solution treated dogs vomited and 93.8% (15/16) of placebo-treated dogs vomited.

The effectiveness of CERENIA administered at 1 mg/kg IV was demonstrated by bridging the results of a PK study to clinical data supporting effectiveness of 1 mg/kg administered SC. The IV and SC administration of a single dose of 1 mg/kg maropitant are equivalent, based on the bioequivalence of the IV and SC AUClast and justification for the therapeutic equivalence of the IV and SC Cmax.

CATS

In a field study, 195 cats were presented to veterinary hospitals with a history of vomiting associated with various clinical conditions including gastroenteritis, gastritis, pancreatitis, inflammatory bowel disease, neoplasia, and hepatic lipidosis. Cats were treated with CERENIA Injectable Solution or placebo (in a ratio of 2:1) and observed in the veterinary hospital for 24 hours for the presence of an emetic event(s) defined as the observation of the act of vomiting or the presence of vomitus. Cats could continue antiemetic treatment every 24 hours for up to 5 consecutive days at the discretion of the clinician. Of 165 cats included in the analysis for effectiveness, 2 CERENIA-treated cats (1.8%) vomited 1 time each and 10 placebo-treated cats (18.5%) vomited a total of 15 times in the first 24 hours post treatment.

Percent of Cats Vomiting for Each Study Day by Treatment
Study Day | Treatment | # cats | # vomited | % vomited
Day 0 | Placebo | 54 | 10 | 18.5
Day 0 | CERENIA | 111 | 2 | 1.8
Day 1 | Placebo | 20 | 4 | 20.0
Day 1 | CERENIA | 34 | 1 | 2.9
Day 2 | Placebo | 9 | 2 | 22.2
Day 2 | CERENIA | 8 | 0 | 0
Day 3 | Placebo | 5 | 0 | 0
Day 3 | CERENIA | 5 | 0 | 0
Day 4 | Placebo | 3 | 0 | 0
Day 4 | CERENIA | 1 | 0 | 0

The effectiveness of CERENIA administered at 1 mg/kg IV was demonstrated by bridging the results of a PK study to clinical data supporting effectiveness of 1 mg/kg administered SC. The IV and SC administration of a single dose of 1 mg/kg maropitant are equivalent, based on the bioequivalence of the IV and SC AUClast and justification for the therapeutic equivalence of the IV and SC Cmax

ANIMAL SAFETY

DOGS

Laboratory and field studies have demonstrated that CERENIA Injectable Solution is well tolerated in dogs after subcutaneous administration.

Fifty six Beagle dogs (28 males and 28 females) approximately 16 weeks of age were administered CERENIA Injectable Solution subcutaneously once daily for 15 days at 0, 1, 3, and 5 mg/kg. There were 8 dogs (4 males and 4 females) in the 1 mg/kg group and 16 dogs (8 males and 8 females) in all other groups. The primary treatment-related findings were injection site reactions. Swelling, thickened skin, or pain at one or more of the injection sites on one or more days of the study were observed in 6 of 16 animals treated with 3 mg/kg/day and 5 of 16 animals treated with 5 mg/kg/day. Additionally, the activated partial thromboplastin time (APTT) was prolonged (67.5 seconds, reference range 9-15 seconds) in one male dog in the 1 mg/kg group on study day 15. Relationship of the prolonged APTT to drug administration could not be determined.

Beagle dogs approximately 8 weeks of age were administered CERENIA Injectable Solution subcutaneously once daily for 15 days at 0, 1, 3, and 5 mg/kg using a protocol similar to the previous study. A dose dependent increase in frequency and severity of bone marrow hypoplasia was observed histologically. One placebo-treated dog died on day 14 of the study and was diagnosed with suppurative pancreatitis and esophagitis. Interpretation of the study results is complicated by the health status of study animals. Dogs used in the study were weaned early, minimally acclimated to the test facility, and many of the dogs in the study tested positive for coccidia.

Beagle dogs approximately 10 weeks of age were administered either placebo tablets for 2 days, CERENIA Tablets at 8 mg/kg for 2 days, placebo (saline) subcutaneously (SC) for 5 days, CERENIA Injectable Solution at 1 mg/kg SC for 5 days, or CERENIA Tablets at 2 mg/kg for 5 days (8 dogs in each dose group). Mild pain associated with injection was noted in more dogs and lasted longer in dogs that received maropitant injections compared to saline. Males administered CERENIA at 8 mg/kg orally for 2 days had a decrease in food consumption. Body weight and food consumption were variable throughout the 4 week acclimatization period. Two dogs that received 8 mg/kg maropitant orally for 2 days were below the reference range for reticulocyte counts. Decreases in reticulocyte counts were also seen in 4 (of 8) placebo treated dogs (SC saline for 5 days). Hypocellular femoral bone marrow described as "minimal" was seen in 1 male that received 1 mg/kg maropitant SC for 5 days; reticulocyte counts were not available for this dog.

Twenty four Beagle dogs approximately 16 weeks of age were administered CERENIA Injectable Solution intravenously once daily for 5 days at 0, 1, and 3 mg/kg (4 females and 4 males per group). CERENIA Injectable Solution was administered at room temperature over 1-2 minutes. Reaction to injection was not specifically recorded. One male dog in the 1 mg/kg group had low hematocrit and white blood cell count on study day 5. One female dog in the 3 mg/kg group had an increased fibrinogen on study day 5. There were no other clinically relevant findings during the study, at necropsy or in histopathology.

CATS

Thirty-two domestic short hair cats (16 males and 16 females) approximately 16 weeks of age were administered CERENIA Injectable Solution subcutaneously once daily for 15 days at 0, 1, 3, and 5 mg/kg. There were 8 cats (4 males and 4 females) in each group. Treatment-related, dose dependent findings included pain associated with injection of CERENIA and injection site heat, pain, redness, and firmness. Pain on injection was observed in 5% of cats at 0 mg/kg, 50% of cats at 1 mg/kg, and 75% of cats at 3 and 5 mg/kg. Injection site firmness >10 mm in diameter was observed at one or more of the injection sites, on one or more days of the study, in 1 of 8 cats at 1 mg/kg, 7 of 8 cats at 3 mg/kg, and 7 of 8 cats at 5 mg/kg. There was a statistically significant reduction (p=0.0171) in food intake at 5 mg/kg compared to cats at 0 mg/kg. One cat at 5 mg/kg was lethargic on Days 12, 13, and 14 of the study. Increased skin turgor was observed in 1 cat at 3 mg/kg on Days 10 and 11, 1 cat at 3 mg/kg on Day 12, and 1 cat at 5 mg/kg on Day 12. At gross necropsy, there were no treatment-related findings. Histopathologic evaluation of injection sites revealed a dose dependent inflammatory response.

Twenty-four healthy domestic shorthair cats (12 males and 12 females) approximately 16 weeks of age were administered maropitant at 1 or 3 mg/kg, or saline at 0.1 mL/kg intravenously once daily for 5 days. CERENIA Injectable Solution was administered at room temperature over 1-2 minutes. Reaction to injection was not specifically recorded, but one cat experienced discomfort with accidental extravascular administration. There were no clinically relevant findings during the study, at necropsy or in histopathology.

STORAGE CONDITIONS

CERENIA Injectable Solution should be stored at or below 30°C (86°F), with excursions permitted up to 40°C (104°F). After first vial puncture, CERENIA Injectable Solution should be stored at refrigerated temperature 2-8°C (36-46°F). Use within 90 days of first vial puncture. Stopper may be punctured a maximum of 25 times.

HOW SUPPLIED

CERENIA Injectable Solution is supplied in 20 mL amber glass vials. Each mL contains 10 mg of maropitant as maropitant citrate.

REFERENCES

1. Diemunsch P, Grelot L. Potential of substance P antagonists as antiemetics. [Review] [60 refs]. Drugs. 2000;60:533-46.

Approved by FDA under NADA # 141-263
zoetis
Distributed by:
Zoetis Inc.
Kalamazoo, MI 49007
Revised: April 2020
40025587